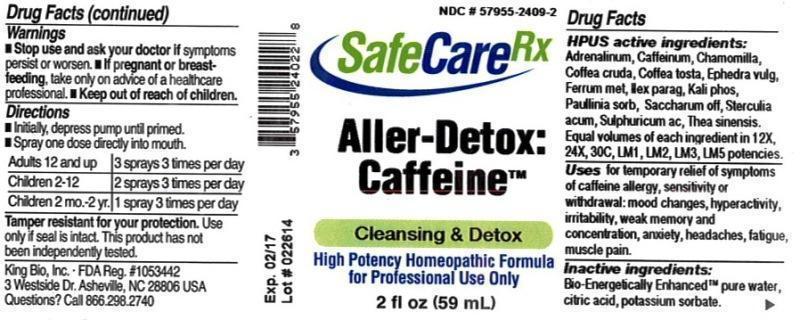 DRUG LABEL: Aller-Detox Caffeine
NDC: 57955-2409 | Form: LIQUID
Manufacturer: King Bio Inc.
Category: homeopathic | Type: HUMAN OTC DRUG LABEL
Date: 20131121

ACTIVE INGREDIENTS: EPINEPHRINE 12 [hp_X]/59 mL; CAFFEINE 12 [hp_X]/59 mL; MATRICARIA RECUTITA 12 [hp_X]/59 mL; ARABICA COFFEE BEAN 12 [hp_X]/59 mL; COFFEA ARABICA SEED, ROASTED 12 [hp_X]/59 mL; EPHEDRA DISTACHYA FLOWERING TWIG 12 [hp_X]/59 mL; IRON 12 [hp_X]/59 mL; ILEX PARAGUARIENSIS LEAF 12 [hp_X]/59 mL; POTASSIUM PHOSPHATE, DIBASIC 12 [hp_X]/59 mL; PAULLINIA CUPANA SEED 12 [hp_X]/59 mL; SUCROSE 12 [hp_X]/59 mL; COLA ACUMINATA SEED 12 [hp_X]/59 mL; SULFURIC ACID 12 [hp_X]/59 mL; GREEN TEA LEAF 12 [hp_X]/59 mL
INACTIVE INGREDIENTS: WATER; CITRIC ACID MONOHYDRATE; POTASSIUM SORBATE

Aller-Detox: Caffeine

Drug Facts

____________________________________________________________________________________________________________________

HPUS active ingredients: Adrenalinum, Caffeinum, Chamomilla, Coffea tosta, Ephedra vulgaris, Ferrum metallicum, Ilex paraguariensis, Kali phosphoricum, Paullinia sorbilis, Saccharum officinale, Sterculia acuminata, Sulphuricum acidum, Thea sinensis. Equal volumes of each ingredient in 12X, 24X, 30C, LM1, LM2, LM3, LM5 potencies.

INDICATIONS AND USAGE

Uses for temporary relief of symptoms of caffeine allergy, sensitivity or withdrawal: mood changes, hyperactivity, irritability, weak memory and concentration, anxiety, headaches, fatigue, muscle pain.

INACTIVE INGREDIENT

Inactive ingredients: Bio-Energetically Enhanced pure water, citric acid, potassium sorbate.

Warnings

- Stop use and ask your doctor if symptoms persist or worsen.
- If pregnant or breast-feeding, take only on advice of a healthcare professional.

- Keep out of reach of children.

Directions:

- Initially, depress pump until primed.
- Spray one dose directly into mouth.
- Adults 12 and up 3 sprays 3 times per day.
- Children 2-12- 2 sprays 3 times per day.
- Children 2 mo.-2yr.- 1 spray 3 times per day.

OTHER SAFETY INFORMATION

Tamper resistant for your protection. Use only if safety seal is intact. This product has not been independently tested.

PURPOSE

Uses for temporary relief of symptoms of caffeine allergy, sensitivity or withdrawal:

- mood changes
- hyperactivity
- irritability
- weak memory and concentration
- anxiety
- headaches
- fatigue
- muscle pain